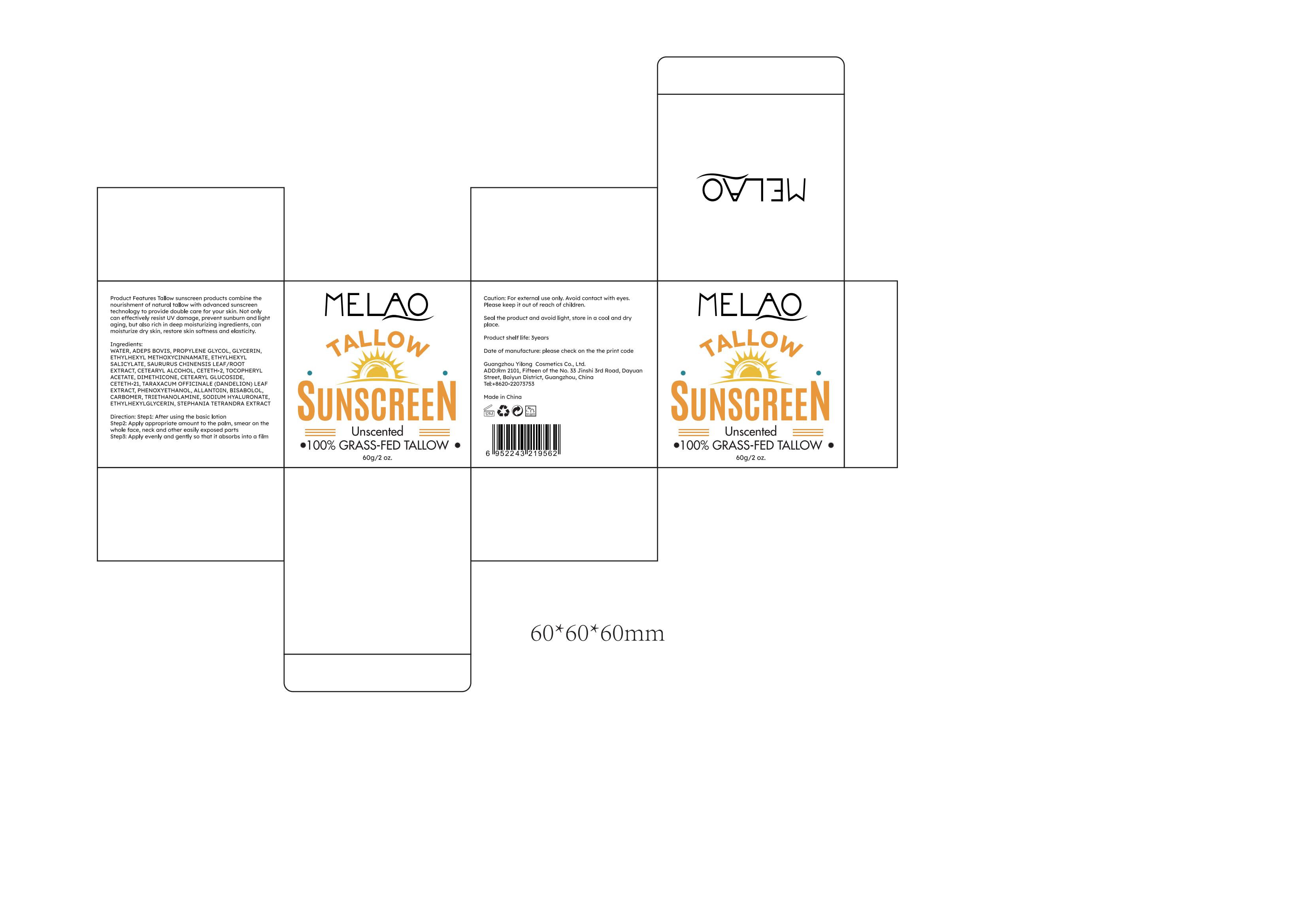 DRUG LABEL: MELAO TALLOW SUNSCREEN
NDC: 60771-0001 | Form: CREAM
Manufacturer: Guangzhou Haishi Biological Technology Co., Ltd.
Category: otc | Type: HUMAN OTC DRUG LABEL
Date: 20241008

ACTIVE INGREDIENTS: PEG-9 DIGLYCIDYL ETHER/SODIUM HYALURONATE CROSSPOLYMER 0.2 g/100 g; .BETA.-BISABOLOL 0.3 g/100 g; TALLOW ACID, BEEF 5 g/100 g; ETHYL METHOXYCINNAMATE 4 g/100 g; SAURURUS CHINENSIS FLOWER 2 g/100 g; STEPHANIA TETRANDRA WHOLE 0.1 g/100 g; TOCOPHERYL RETINOATE 1 g/100 g
INACTIVE INGREDIENTS: DIPROPYLENE GLYCOL; ALLANTOIN; GLYCERIN

MELAO TALLOW SUNSCREEN

Active ingredients

ETHYLHEXYL METHOXYCINNAMATE 4%

SODIUM HYALURONATE 0.2%
BISABOLOL 0.3%
ADEPS BOVIS 5%
TOCOPHERYL ACETATE 1%

SAURURUS CHINENSIS LEAF/ROOT EXTRACT 2%
STEPHANIA TETRANDRA EXTRACT 0.1%

Purpose

sunscreen

Uses

Step1: After using the basic lotion
Step2: Apply appropriate amount to the palm, smear on the whole face, neck and other easily exposed parts
Step3: Apply evenly and gently so that it absorbs into a film

Warnings

For external use only.

Stop use and ask a doctor if

rash occurs.

Do not use

on damaged or broken skin.

When using this product

keep out of eyes. Rinse with water to remove.

Keep out of reach of children.

If swallowed, get medical help or contact a Poison Control Center right away.

Dosage

Squeeze out an appropriate amount of sunscreen and spread evenly on skin.

Inactive ingredients

WATER 67.6%
PROPYLENE GLYCOL 4%
GLYCERIN 4%
ALLANTOIN 0.3%
DIMETHICONE 1%
CETEARYL GLUCOSIDE 1%
CETETH-21 0.8%
CETETH-2 1.3%
CETEARYL ALCOHOL 1.5%
CARBOMER 0.3%
TRIETHANOLAMINE 0.3%
PHENOXYETHANOL 0.4%
ETHYLHEXYLGLYCERIN 0.1%
TARAXACUM OFFICINALE (DANDELION) LEAF EXTRACT 0.8%

ETHYLHEXYL SALICYLATE 4%